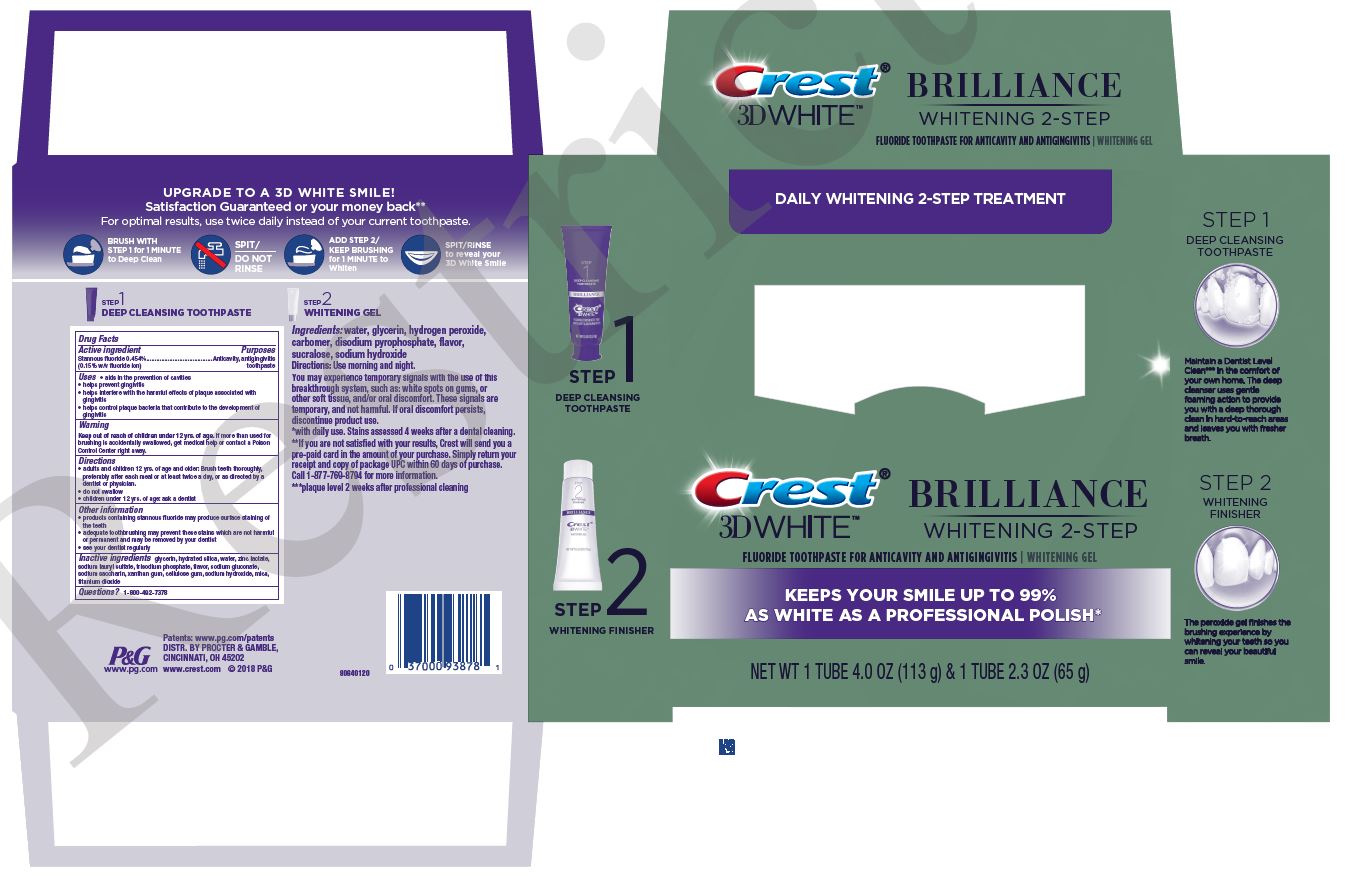 DRUG LABEL: Crest 3D White Brilliance
NDC: 37000-863 | Form: KIT | Route: DENTAL
Manufacturer: The Procter & Gamble Manufacturing Company
Category: otc | Type: HUMAN OTC DRUG LABEL
Date: 20250114

ACTIVE INGREDIENTS: STANNOUS FLUORIDE 1.5 mg/1 g
INACTIVE INGREDIENTS: GLYCERIN; HYDRATED SILICA; WATER; ZINC LACTATE; SODIUM LAURYL SULFATE; SODIUM GLUCONATE; SACCHARIN SODIUM; XANTHAN GUM; CARBOXYMETHYLCELLULOSE SODIUM; SODIUM HYDROXIDE; MICA; TITANIUM DIOXIDE

Crest® 3D White™ Brilliance
Daily Cleansing and Whitening System

Drug Facts

Active ingredient

Stannous fluoride 0.454% (0.15% w/v fluoride ion)

Purposes

Anticavity, antigingivitis toothpaste

Uses

- aids in the prevention of cavities
- helps prevent gingivitis
- helps interfere with the harmful effects of plaque associated with gingivitis
- helps control plaque bacteria that contribute to the development of gingivitis

Warning

Keep out of reach of children under 12 yrs. of age. If more than used for brushing is accidentally swallowed, get medical help or contact a Poison Control Center right away.

Directions

- adults and children 12 yrs. of age and older: Brush teeth thoroughly, preferably after each meal or at least twice a day, or as directed by a dentist or physician.
- do not swallow
- children under 12 yrs. of age: ask a dentist

Other information

- products containing stannous fluoride may produce surface staining of the teeth
- adequate toothbrushing may prevent these stains which are not harmful or permanent and may be removed by your dentist
- see your dentist regularly

Inactive ingredients

glycerin, hydrated silica, water, zinc lactate, sodium lauryl sulfate, trisodium phosphate, flavor, sodium gluconate, sodium saccharin, xanthan gum, cellulose gum, sodium hydroxide, mica, titanium dioxide

Questions?

1 (800) 492-7378

DISTR. BY PROCTER & GAMBLE,
CINCINNATI, OH 45202

PRINCIPAL DISPLAY PANEL - Kit Carton

DAILY WHITENING 2-STEP TREATMENT

Crest BRILLIANCE

3D WHITE WHITENING 2-STEP

FLUORIDE TOOTHPASTE FOR ANTICAVITY AND ANTIGINGIVITIS - WHITENING GEL

KEEPS YOUR SMILE UP TO 99%

AS WHITE AS A PROFESSIONAL POLISH

NET WT 1 TUBE 4.0 OZ (113 g) & 1 TUBE 2.3 OZ (65 g)